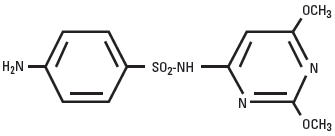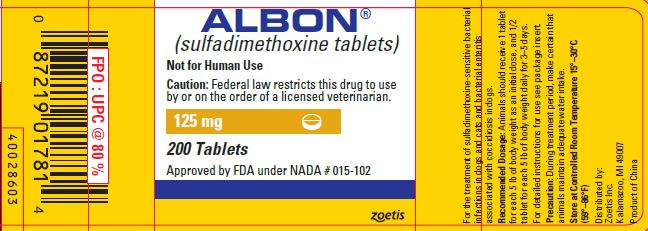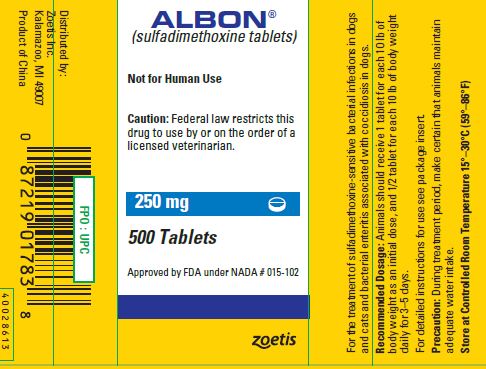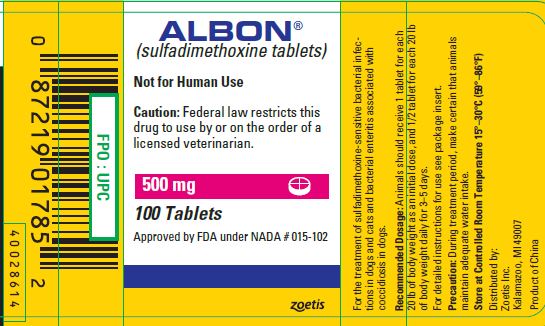 DRUG LABEL: Albon
NDC: 54771-8431 | Form: TABLET
Manufacturer: Zoetis Inc.
Category: animal | Type: PRESCRIPTION ANIMAL DRUG LABEL
Date: 20191107

ACTIVE INGREDIENTS: SULFADIMETHOXINE 125 mg/1 1

ALBON® Tablets

ALBON®
(sulfadimethoxine tablets)
Tablets

For the treatment of sulfadimethoxine-sensitive bacterial infections in dogs and cats and bacterial enteritis associated with coccidiosis in dogs.

CAUTION

Federal law restricts this drug to use by or on the order of a licensed veterinarian.

Description

Albon is a low-dosage, rapidly absorbed, long-acting sulfonamide, effective for the treatment of a wide range of bacterial infections commonly encountered in dogs and cats.

Sulfadimethoxine is a white, almost tasteless and odorless compound. Chemically, it is N^1-(2,6-dimethoxy-4-pyrimidinyl) sulfanilamide. The structural formula is:

Action

Sulfadimethoxine has been demonstrated clinically or in the laboratory to be effective against a variety of organisms, such as streptococci, klebsiella, proteus, shigella, staphylococci, escherichia, and salmonella.^1,2 These organisms have been demonstrated in respiratory, genitourinary, enteric, and soft tissue infections of dogs and cats.

The systemic sulfonamides which include sulfadimethoxine are bacteriostatic agents. Sulfonamides competitively inhibit bacterial synthesis of folic acid (pteroylglutamic acid) from para-aminobenzoic acid. Mammalian cells are capable of utilizing folic acid in the presence of sulfonamides.

The tissue distribution of sulfadimethoxine, as with all sulfonamides, is a function of plasma levels, degree of plasma protein binding, and subsequent passive distribution in the tissues of the lipid-soluble un-ionized form. The relative amounts are determined by both its pKa and by the pH of each tissue. Therefore, levels tend to be higher in less acid tissue and body fluids or those diseased tissues having high concentrations of leucocytes.^2

In the dog, sulfadimethoxine is not acetylated as in most other animals, and it is excreted predominantly as the unchanged drug.^3 Sulfadimethoxine has a relatively high solubility at the pH normally occurring in the kidney, precluding the possibility of precipitation and crystalluria. Slow renal excretion results from a high degree of tubular reabsorption,^4 and plasma protein binding is very high, providing a blood reservoir of the drug. Thus, sulfadimethoxine maintains higher blood levels than most other long-acting sulfonamides. Single, comparatively low doses of Albon give rapid and sustained therapeutic blood levels.^1

To assure successful sulfonamide therapy (1) the drug must be given early in the course of the disease, and it must produce a high sulfonamide level in the body rapidly after administration, (2) therapeutically effective sulfonamide levels must be maintained in the body throughout the treatment period, (3) treatment should continue for a short period of time after the clinical signs have disappeared, and (4) the causative organisms must be sensitive to this class of drugs.

INDICATIONS AND USAGE

Albon is indicated for the treatment of respiratory, genitourinary tract, enteric, and soft tissue infections in dogs and cats:

tonsillitis
pharyngitis
bronchitis
pneumonia
cystitis
nephritis
metritis
pyometra

pustular dermatitis
anal gland infections
abscesses
wound infections
bacterial enteritis
canine salmonellosis
bacterial enteritis associated
with coccidiosis in dogs

when caused by streptococci, staphylococci, escherichia, salmonella, klebsiella, proteus or shigella organisms sensitive to sulfadimethoxine.

Limitations: Sulfadimethoxine is not effective in viral or rickettsial infections, and as with any antibacterial agent, occasional failures in therapy may occur due to resistant microorganisms. The usual precautions in sulfonamide therapy should be observed.

WARNING

Not for human use.

PRECAUTION

During treatment period, make certain that animals maintain adequate water intake.

If animals show no improvement within 2 or 3 days, reevaluate your diagnosis.

DOSAGE AND ADMINISTRATION

Initial Dose: 25 mg/lb (55 mg/kg) of animal body weight.

Subsequent Daily Doses: 12.5 mg/lb (27.5 mg/kg) of animal body weight.

For ease of administration in animals of varying weights, 3 tablet sizes are provided. The following table indicates how dosage may be adjusted depending on tablet size and body weight. Subsequent doses should be given at 24-hour intervals.

Tablet Size | Approximate Animal Weight | Initial Dose 25 mg/lb (55 mg/kg) | Subsequent Daily Doses 12.5 mg/lb (27.5 mg/kg)
125 mg | 5 lb (2.2 kg) | 1 tablet | 1/2 tablet
250 mg | 10 lb (4.5 kg) | 1 tablet | 1/2 tablet
500 mg | 20 lb (9.1 kg) | 1 tablet | 1/2 tablet

Treatment may be initiated with Albon Injection 40% to obtain effective blood levels almost immediately or to facilitate treatment of the fractious animal.

Length of treatment depends on the clinical response. In most cases treatment for 3–5 days is adequate. Treatment should be continued until the animal is asymptomatic for 48 hours.

TOXICITY AND SAFETY

Data regarding acute and chronic toxicities of sulfadimethoxine indicate the drug is very safe. The LD50 in mice is greater than 2 g/kg of body weight when administered intraperitoneally and greater than 16 g/kg when administered orally. In dogs receiving massive single oral doses of 3.2 g/kg of body weight, diarrhea was the only adverse effect observed. Dogs given 160 mg/kg of body weight orally daily for 13 weeks showed no signs of toxicity.

STORAGE

Store at controlled room temperature 15°–30°C (59°–86°F).

HOW SUPPLIED

Albon Tablets are available in the following strengths for dogs and cats: 125 mg, 250 mg, or 500 mg sulfadimethoxine per tablet.

REFERENCES

1. Data on file, Pfizer Animal Health.

2. Stowe CM: The sulfonamides. In Jones LM (ed), Veterinary Pharmacology and Therapeutics, Ames, Iowa, Iowa State University Press, chapter 33, 1965.

3. Bridges JW, Kirby MR, Walker SR, et al: Species differences in the metabolism of sulfadimethoxine. Biochem J 109:851, 1968.

4. Baggot JD: Some aspects of drug persistence in domestic animals. Res Vet Sci 11(2):130, 1970.

Approved by FDA under NADA # 015-102

zoetis

Distributed by:
Zoetis Inc.
Kalamazoo, MI 49007

40028552
Revised: August 2019